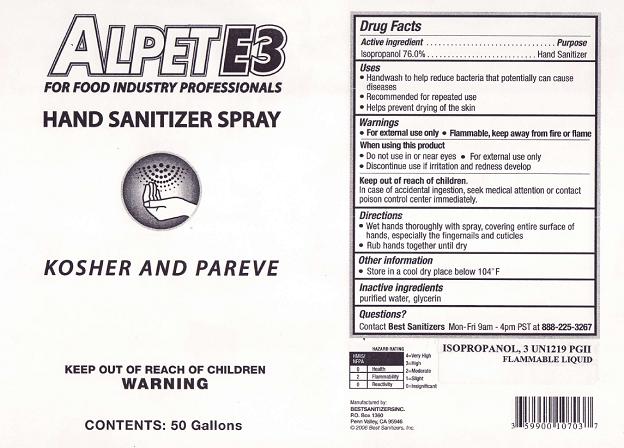 DRUG LABEL: Alpet E3 Hand Sanitizer Spray
NDC: 59900-107 | Form: LIQUID
Manufacturer: Best Sanitizer, Inc.
Category: otc | Type: HUMAN OTC DRUG LABEL
Date: 20100419

ACTIVE INGREDIENTS: Isopropyl Alcohol 760 g/1000 mL

Drug Facts

Active Ingredient

Isopropanol 76.0%

Purpose

Hand Sanitizer

Uses

- Handwash to help reduce bacteria that potentially can cause diseases
- Recommended for repeated use
- Helps prevent drying of the skin

Warnings

- For external use only
- Flammable, keep away from fire or flame

When using this product

- Do not use in or near eyes
- For external use only
- Discontinue use if irritation and redness develop

Keep out of reach of children

In case of accidental ingestion, seek medical attention or contact a poison control center immediately.

Directions

- Wet hands thoroughly with spray, covering entire surface of hands, especially the fingernails and cuticles
- Rub hands together until dry

Other information

- Store in a cool dry place below 104° F

Inactive ingredients

purified water, glycerin

Questions?

Contact Best Sanitizers Mon-Fri 9am - 4p PST at 888-225-3267

Principal Display Panel

NDC: 59900-107-02

NDC: 59900-107-03

NDC: 59900-107-04

NDC: 59900-107-05

NDC: 59900-107-06

Alpet E3

for food industry professionals

Hand Sanitizer Spray